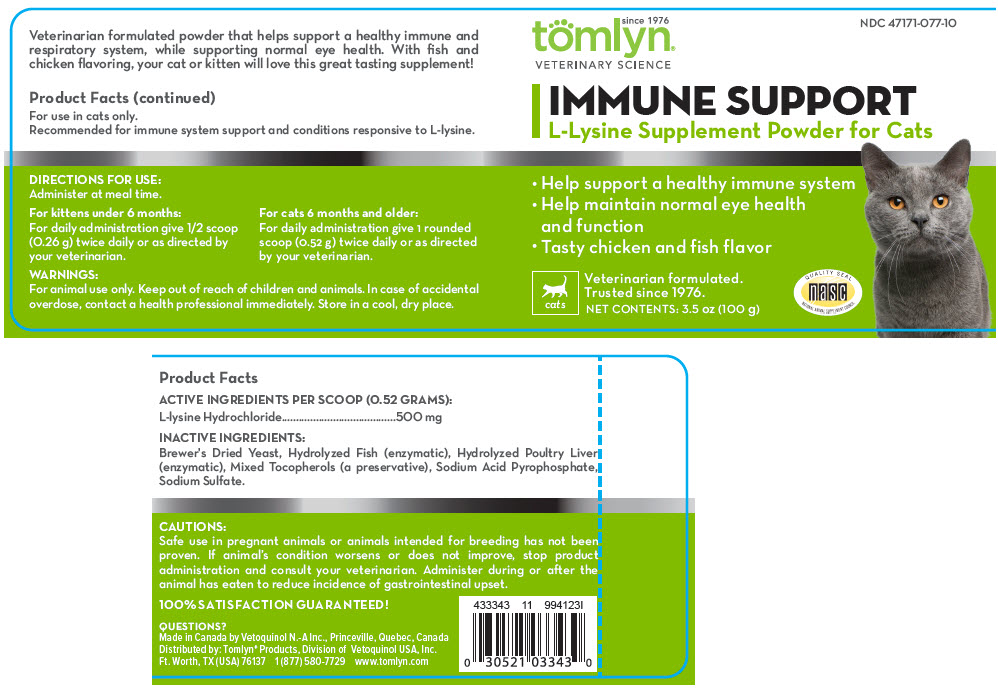 DRUG LABEL: IMMUNE SUPPORT
NDC: 47171-077 | Form: POWDER
Manufacturer: Tomlyn Products, a Divison of Vetoquinol USA, Inc.
Category: animal | Type: OTC ANIMAL DRUG LABEL
Date: 20200214

ACTIVE INGREDIENTS: LYSINE HYDROCHLORIDE 500 mg/0.52 g
INACTIVE INGREDIENTS: SACCHAROMYCES CEREVISIAE; TOCOPHEROL; SODIUM ACID PYROPHOSPHATE; SODIUM SULFATE

IMMUNE SUPPORT

Product Facts

DESCRIPTION

ACTIVE INGREDIENTS PER SCOOP (0.52 GRAMS):

L-lysine Hydrochloride | 500 mg

INACTIVE INGREDIENTS:

Brewer's Dried Yeast, Hydrolyzed Fish (enzymatic), Hydrolyzed Poultry Liver (enzymatic), Mixed Tocopherols (a preservative), Sodium Acid Pyrophosphate, Sodium Sulfate.

VETERINARY INDICATIONS

Veterinarian formulated powder that helps support a healthy immune and respiratory system, while supporting normal eye health. With fish and chicken flavoring, your cat or kitten will love this great tasting supplement!

For use in cats only.

Recommended for immune system support and conditions responsive to L-lysine.

DIRECTIONS FOR USE:

Administer at meal time.

For kittens under 6 months:

For daily administration give 1/2 scoop (0.26 g) twice daily or as directed by your veterinarian.

For cats 6 months and older:

For daily administration give 1 rounded scoop (0.52 g) twice daily or as directed by your veterinarian.

WARNINGS:

For animal use only. Keep out of reach of children and animals. In case of accidental overdose, contact a health professional immediately. Store in a cool, dry place.

CAUTIONS:

Safe use in pregnant animals or animals intended for breeding has not been proven. If animal's condition worsens or does not improve, stop product administration and consult your veterinarian. Administer during or after the animal has eaten to reduce incidence of gastrointestinal upset.

100% SATISFACTION GUARANTEED!

QUESTIONS?

Made in Canada by Vetoquinol N.-A Inc., Princeville, Quebec, Canada
Distributed by: Tomlyn® Products, Division of Vetoquinol USA, Inc.
Ft. Worth, TX (USA) 76137 1 (877) 580-7729 www.tomlyn.com

PRINCIPAL DISPLAY PANEL - 100 g Container Label

since 1976
tomlyn®
VETERINARY SCIENCE
NDC 47171-077-10

IMMUNE SUPPORT
L-Lysine Supplement Powder for Cats

- Help support a healthy immune system
- Help maintain normal eye health
  and function
- Tasty chicken and fish flavor

cats
Veterinarian formulated.
Trusted since 1976.
NET CONTENTS: 3.5 oz (100 g)
QUALITY SEAL
nasc
NATIONAL ANIMAL SUPPLEMENT COUNCIL